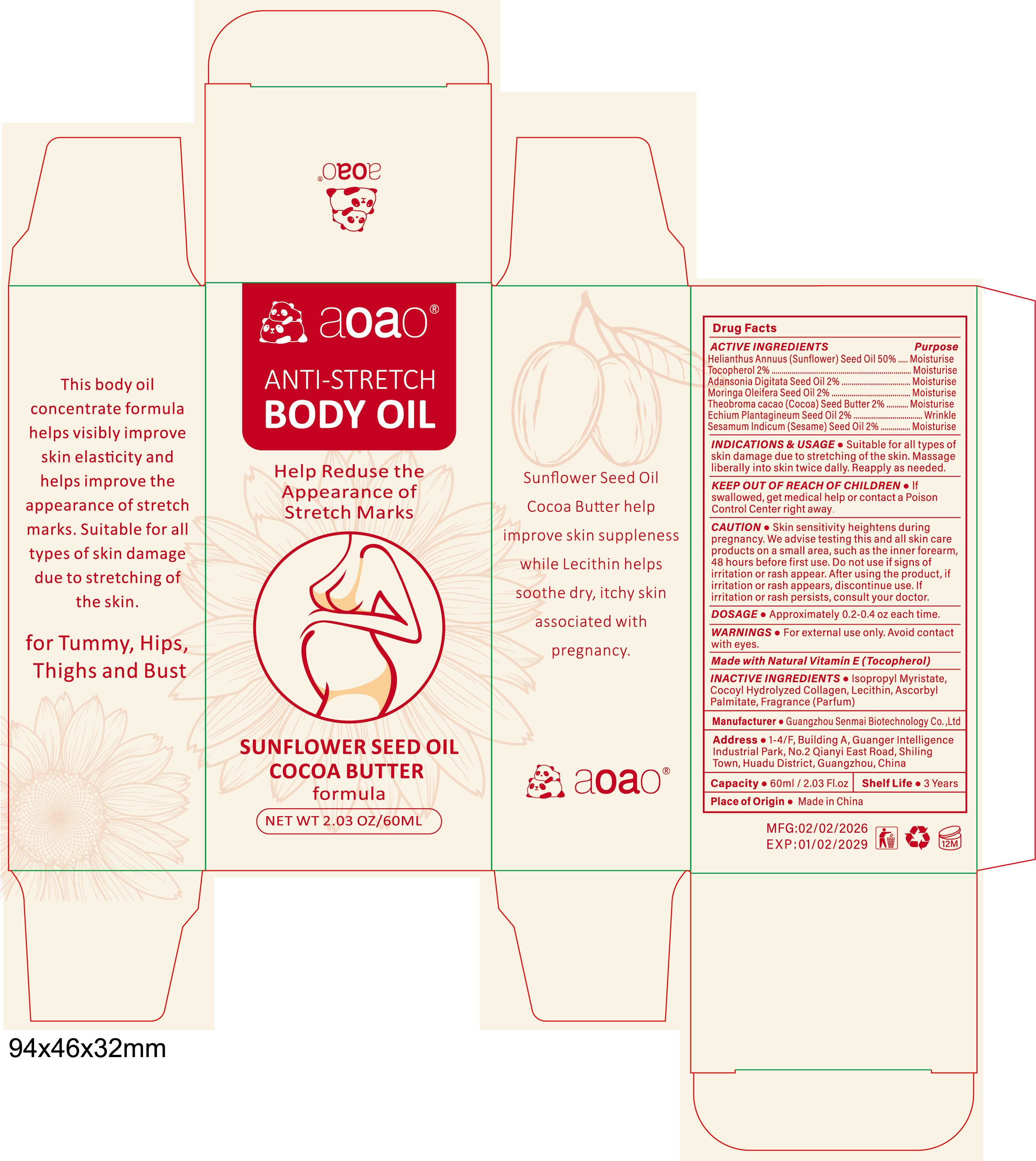 DRUG LABEL: Body Oil for Stretch Marks
NDC: 84509-101 | Form: OIL
Manufacturer: Dongguan Xiaogoubeige trading company Ltd.
Category: otc | Type: HUMAN OTC DRUG LABEL
Date: 20260127

ACTIVE INGREDIENTS: SUNFLOWER OIL 30000 mg/60 mL; TOCOPHEROL 1200 mg/60 mL; ADANSONIA DIGITATA SEED OIL 1200 mg/60 mL; SESAME OIL 1200 mg/60 mL; ECHIUM PLANTAGINEUM SEED OIL 1200 mg/60 mL; MORINGA OLEIFERA SEED OIL 1200 mg/60 mL; COCOA BUTTER 1200 mg/60 mL
INACTIVE INGREDIENTS: LECITHIN, SUNFLOWER; FRAGRANCE 13576; SURFACTIN; ASCORBYL PALMITATE; ISOPROPYL MYRISTATE

Active Ingredients

Helianthus Annuus (Sunflower) Seed 0il 50%
Tocopherol 2%
Adansonia Digitata Seed 0il 2%
Moringa Oleifera Seed 0il 2%
Theobroma cacao (Cocoa) Seed Butter 2%
Echium Plantagineum Seed Oil 2%
Sesamum Indicum (Sesame) Seed 0il 2%

Purpose

Moisturise, Wrinkle

INDICATIONS & USAGE

Suitable for all types of skin damage due to stretching of the skin.Massage liberally into skin twice dally. Reapply as needed.

KEEP OUT OF REACH OF CHILDREN

lf swallowed, get medical help or contact a Poison Control Center right away.

CAUTION

Skin sensitivity heightens during pregnancy. We advise testing this and all skin care products on a small area, such as the inner forearm,48 hours before first use. Do not use if signs of irritation or rash appear. After using the product, if irritation or rash appears, discontinue use. lf irritation or rash persists, consult your doctor.

DOSAGE

Approximately 0.2-0.4 oz each time.

WARNINGS

For external use only. Keep out of reach of children.Avoid contact with eyes.

DESCRIPTION

Made with Natural Vitamin E (Tocopherol)

Inactive Ingredients

Isopropyl Myristate,Cocoyl Hydrolyzed Collagen, Lecithin, Ascorbyl Palmitate, Fragrance (Parfum)

Manufacturer

Guangzhou Senmai Biotechnology Co.,Ltd

Address

1-4/F, Building A, Guanger Intelligence Industrial Park, No.2 Qianyi East Road, Shiling Town, Huadu District, Guangzhou, China

Capacity

60ml/2.03 Fl.oz

Shelf Life

3 Years

Place of Origin

Made in China